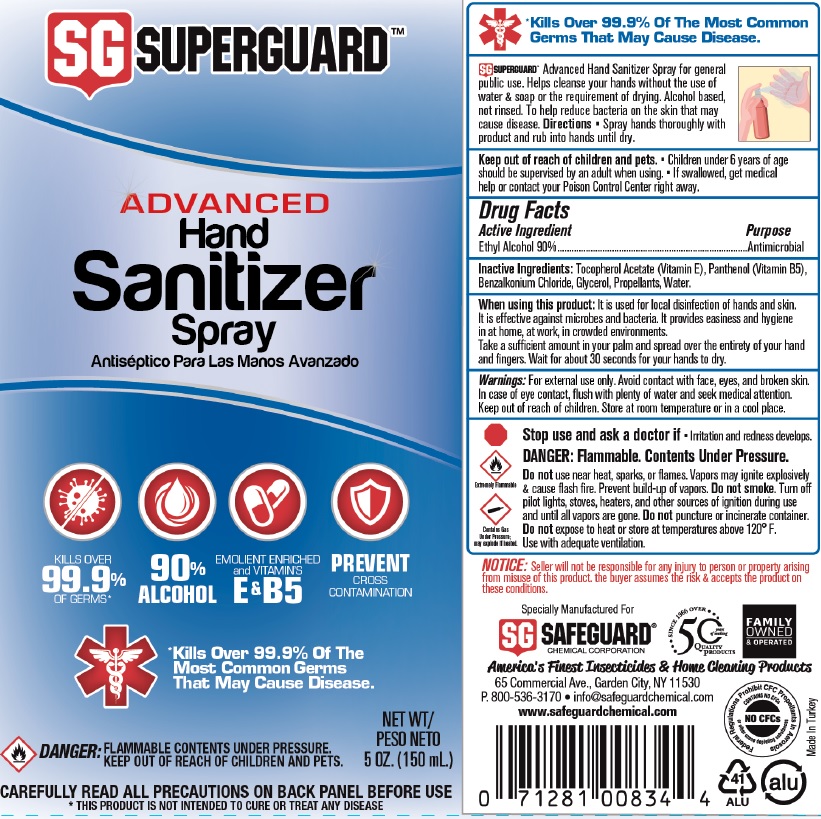 DRUG LABEL: Superguard Advanced Hand Sanitizer
NDC: 40099-000 | Form: AEROSOL, SPRAY
Manufacturer: Safeguard Chemical Corporation
Category: otc | Type: HUMAN OTC DRUG LABEL
Date: 20220713

ACTIVE INGREDIENTS: ALCOHOL 0.9 mL/1 mL
INACTIVE INGREDIENTS: ISOBUTANE; PROPANE; BUTANE; .ALPHA.-TOCOPHEROL ACETATE; PANTHENOL; BENZALKONIUM CHLORIDE; GLYCERIN; WATER

Superguard Advanced Hand Sanitizer Spray

Active Ingredient

Ethyl Alcohol 90%

Purpose

Antimicrobial

Inactive Ingredients:

Tocopherol Acetate (Vitamin E), Panthenol (Vitamin B5), Benzalkonium Chloride, Glycerol, Propellants, Water.

INDICATIONS AND USAGE

Advanced Hand Sanitizer Spray for general public use. Helps cleanse your hands without the use of water & soap or the requirement of drying. Alcohol based, not rinsed. To help reduce bacteria on the skin that may cause disease.

Warnings:

For external use only. Avoid contact with face, eyes and broken skin. In case of eye contact, flush with plenty of water and seek medical attention. Keep out of reach of children. Store at room temperature or in a cool place.

When using this product:

It is used for local disinfection of hands and skin. It is effective against microbes and bacteria. It provides easiness and hygiene in at home, at work, in crowded environments.

Take a sufficient amount in your palm and spread over the entirety of your hand and fingers. Wait for about 30 seconds for your hands to dry.

Stop use and ask a doctor if

Irritation and redness develops.

DANGER: Flammable. Contents Under Pressure.

Do not use

near heat, sparks, or flames, Vapors may ignite explosively & cause flash fire. Prevent build-up of vapors. Do not smoke. Turn off pilot lights, stoves, heaters, and other sources of ignition during use and until all vapors are gone. Do not puncture or incinerate container.

Keep out of reach of children and pets.

- Children under 6 years of age should be supervised by an adult when using.
- If swallowed, get medical help or contact your Poison Control Center right away.

Directions

Spray hands thoroughly with product and rub into hands until dry.

Do not expose to heat or store at temperatures above 120° F. Use with adequate ventilation.